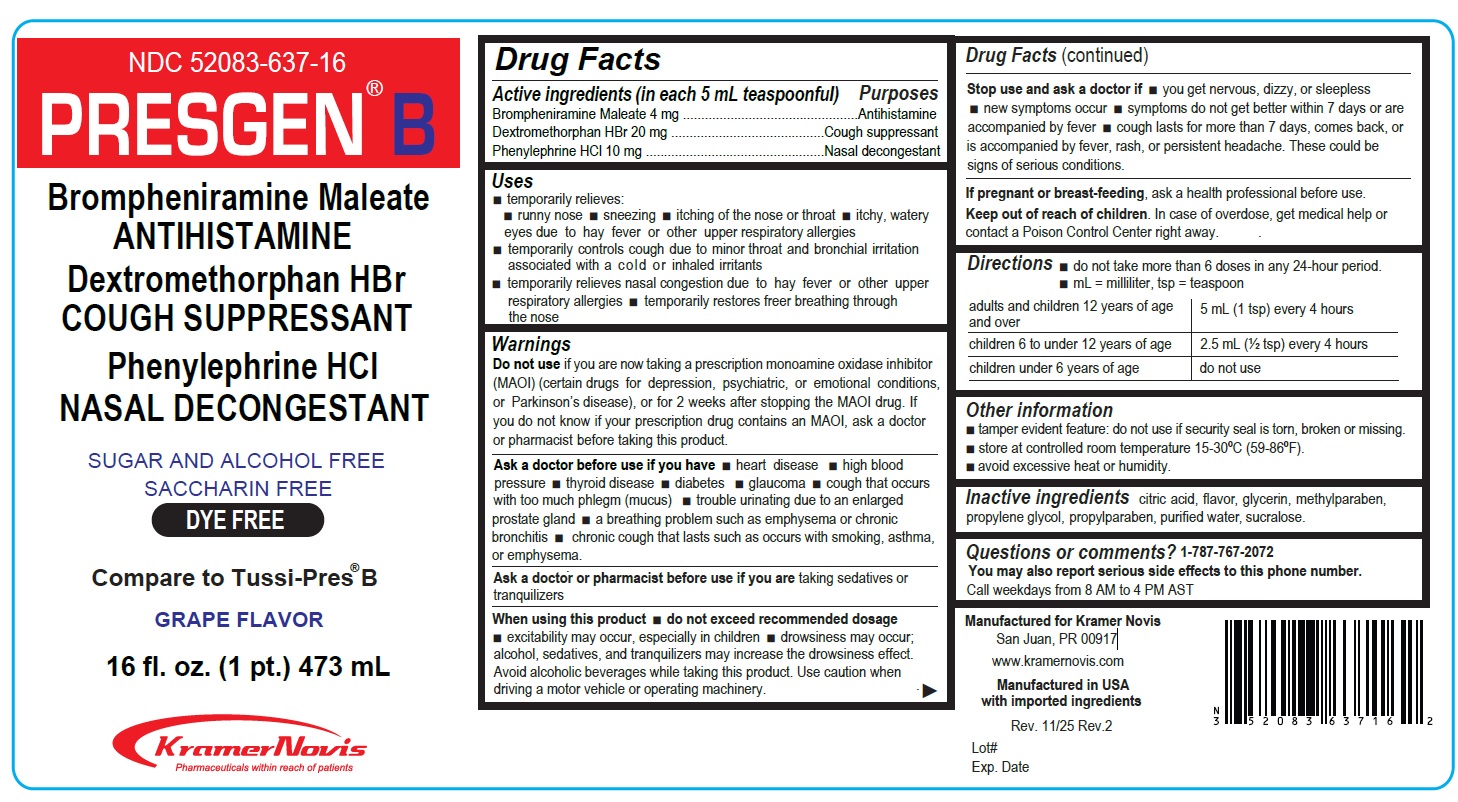 DRUG LABEL: Presgen B
                
NDC: 52083-637 | Form: SYRUP
Manufacturer: KRAMER NOVIS
Category: otc | Type: HUMAN OTC DRUG LABEL
Date: 20251203

ACTIVE INGREDIENTS: BROMPHENIRAMINE MALEATE 4 mg/5 mL; DEXTROMETHORPHAN HYDROBROMIDE 20 mg/5 mL; PHENYLEPHRINE HYDROCHLORIDE 10 mg/5 mL
INACTIVE INGREDIENTS: CITRIC ACID MONOHYDRATE; GLYCERIN; METHYLPARABEN; PROPYLENE GLYCOL; PROPYLPARABEN; WATER; SUCRALOSE

PRESGEN® B

Active Ingredients (in each 5 mL teaspoonful)

Brompheniramine Maleate 4 mg
Dextromethorphan HBr 20 mg
Phenylephrine HCl 10 mg

Purposes

Antihistamine
Cough suppressant
Nasal decongestant

Uses

• temporarily relieves:
• runny nose • sneezing • itching of the nose or throat • itchy, watery eyes due to hay fever or other upper respiratory allergies
• temporarily controls cough due to minor throat and bronchial irritation associated with a cold or inhaled irritants
• temporarily relieves nasal congestion due to hay fever or other upper respiratory allergies • temporarily restores freer breathing through the nose

Warnings

Do not use if you are now taking a prescription monoamine oxidase inhibitor (MAOI) (certain drugs for depression, psychiatric, or emotional conditions, or Parkinson's disease), or for 2 weeks after stopping the MAOI drug. If you do not know if your prescription drug contains an MAOI, ask a doctor or pharmacist before taking this product.

Ask a doctor before use if you have • heart disease • high blood pressure • thyroid disease • diabetes • glaucoma • cough that occurs with too much phlegm (mucus) • trouble urinating due to an enlarged prostate gland • a breathing problem such as emphysema or chronic bronchitis • chronic cough that lasts such as occurs with smoking, asthma, or emphysema.

Ask a doctor or pharmacist before use if you are taking sedatives or tranquilizers.

When using this product • do not exceed recommended dosage
• excitability may occur, especially in children • drowsiness may occur; alcohol, sedatives, and tranquilizers may increase the drowsiness effect. Avoid alcoholic beverages while taking this product. Use caution when driving a motor vehicle or operating machinery.

Stop use and ask a doctor if • you get nervous, dizzy, or sleepless • new symptoms occur • symptoms do not get better within 7 days or are accompanied by fever • coughs lasts for more than 7 days, comes back, or is accompanied by fever, rash, or persistent headache. These could be signs of serious conditions.

If pregnant or breast-feeding, ask a health professional before use.

Keep out of reach of children. In case of overdose, get medical help or contact a Poison Control Center right away.

Directions

• do not take more than 6 doses in any 24-hour period.
• mL = milliliter, tsp = teaspoon

adults and children 12 years of age and over | 5 mL (1 tsp) every 4 hours
children 6 to under 12 years of age | 2.5 mL (½ tsp) every 4 hours
children under 6 years of age | do not use

Other information

• tamper evident feature: do not use if security seal is torn, broken or missing.
• store at controlled room temperature 15-30°C (59-86°F).
• avoid excessive heat or humidity.

Inactive ingredients

citric acid, flavor, glycerin, methylparaben, propylene glycol, propylparaben, purified water, sucralose.

Questions or comments?1-787-767-2072

You may also report serious side effects to this phone number.
Call weekdays from 8 AM to 4 PM AST

Brompheniramine Maleate
ANTIHISTAMINE

Dextromethorphan HBr
COUGH SUPPRESSANT

Phenylephrine HCl
NASAL DECONGESTANT

SUGAR AND ALCOHOL FREE

SACCHARINE FREE

DYE FREE

Compare to Tussi-Press®B

GRAPE FLAVOR

Kramer Novis
Pharmaceuticals within reach of patients

Manufactured for Kramer Novis
San Juan, PR 00917

www.kramernovis.com

Manufactured in the USA with imported ingredients